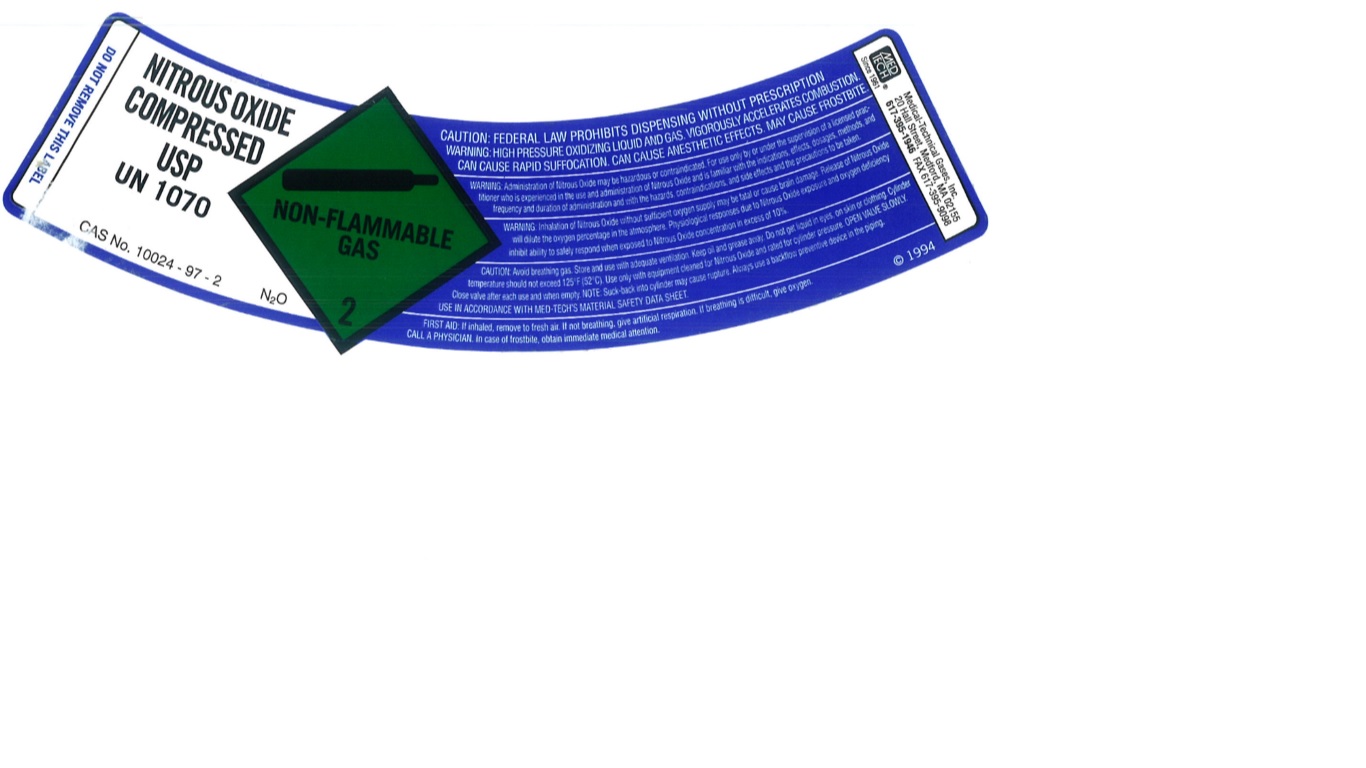 DRUG LABEL: Nitrous Oxide
NDC: 10736-017 | Form: GAS
Manufacturer: MEDICAL-TECHNICAL GASES, INC.
Category: prescription | Type: HUMAN PRESCRIPTION DRUG LABEL
Date: 20251125

ACTIVE INGREDIENTS: NITROUS OXIDE 995 mL/1 L

Nitrous Oxide Label

DO NOT REMOVE THIS LABEL
NITROUS OXIDE COMPRESSED USP
UN1070
CAS No. 10024-97-2 N2O
CAUTION: FEDERAL LAW PROHIBITS DISPENSING WITHOUT PRESCRIPTION
WARNING: HIGH PRESSURE OXIDIZING LIQUID AND GAS. VIGOROUSLY ACCELERATES COMBUSTION. CAN CAUSE RAPID SUFFOCATION. CAN CAUSE ANESTHETIC EFFECTS. MAY CAUSE FROSTBITE.
WARNING: Administration of Nitrous Oxide may be hazardous or contraindicated. For use only by or under the supervision of a licensed practitioner who is experienced in the use and administration of Nitrous Oxide and is familiar with the indications, effects, dosages, methods, and frequency and duration of administration and with the hazards, contraindications, and side effects and the precautions to be taken.
WARNING: Inhalation of Nitrous Oxide without sufficient oxygen supply may be fatal or cause brain damage. Release of Nitrous Oxide will dilute the oxygen percentage in the atmosphere. Physiological responses due to Nitrous Oxide exposure and oxygen deficiency inhibit ability to safely respond when exposed to Nitrous Oxide concentration in excess of 10 percent.
CAUTION: Avoid breathing gas. Store and use with adequate ventilation. Keep oil and grease away. Do not get liquid in eyes, on skin or clothing. Cylinder temperature should not exceed 125 F (52 C). Use only with equipment cleaned for Nitrous Oxide and rated for cylinder pressure. OPEN VALVE SLOWLY. USE IN ACCORDANCE WITH MED-TECH’S MATERIALS SAFETY DATA SHEET.
FIRST AID: If inhaled, remove to fresh air. If not breathing, give artificial respiration. If breathing is difficult, give oxygen.
CALL A PHYSICIAN. In case of frostbite, obtain immediate medical attention.
MEDTECH Since 1961
MEDICAL-TECHNICAL GASES, INC.
20 Hall Street, Medford, MA 02155
617-395-1946 FAX 617-395-9098